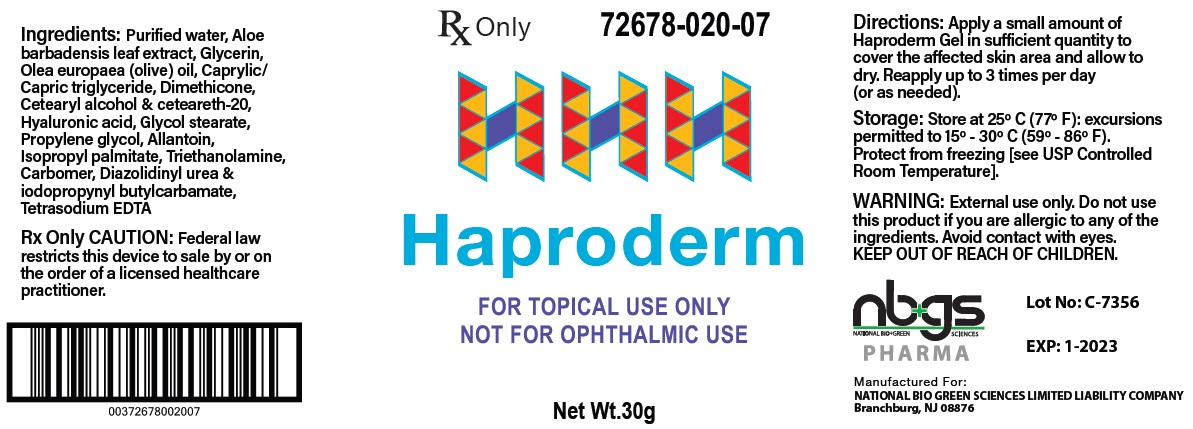 DRUG LABEL: Haproderm Wound Gel Dressing with Hyaluronic Acid
NDC: 72678-020
Manufacturer: NATIONAL BIO GREEN SCIENCES LIMITED LIABILITY COMPANY
Category: other | Type: PRESCRIPTION MEDICAL DEVICE LABEL
Date: 20210727
INACTIVE INGREDIENTS: WATER; ALOE VERA LEAF; GLYCERIN; OLIVE OIL; MEDIUM-CHAIN TRIGLYCERIDES; DIMETHICONE; CETOSTEARYL ALCOHOL; POLYOXYL 20 CETOSTEARYL ETHER; HYALURONIC ACID; GLYCOL STEARATE; PROPYLENE GLYCOL; ALLANTOIN; ISOPROPYL PALMITATE; TROLAMINE; CARBOMER HOMOPOLYMER, UNSPECIFIED TYPE; DIAZOLIDINYL UREA; IODOPROPYNYL BUTYLCARBAMATE; EDETATE SODIUM

Haproderm

DESCRIPTION: Haproderm is a soothing wound gel that is formulated for the dressing and management of superficial wounds, minor abrasions, pressure ulcers stage II - IV, 1st and 2nd degree burns, including sunburns, and radiation dermatitis. When applied properly to a wound hyaluronic acid adheres to tissue to prevent damage while supplying moisture to the cells. Medium molecular weight polysaccharides in aloe Vera moisturize and reduce inflammation. Proven therapeutic moisturizers, lipids, glycerin and allantoin, relieves dryness

INDICATIONS FOR USE

Under the supervision of a healthcare professional, Haproderm Gel is indicated to manage and relieve the burning, itching and pain experienced with various types of dermatoses, including atopic dermatitis, allergic contact dermatitis and radiation dermatitis. Haproderm Gel also helps to relieve dry, waxy skin by maintaining a moist wound and skin environment, which is beneficial to the healing process.

DESCRIPTION

Haproderm Gel is a non-sterile, off-white, low odor, fragrance free, topical product. The Haproderm Gel forms a physical barrier that helps to maintain a moist wound and skin environment. Haproderm Gel is a prescription medical device.

CONTRAINDICATIONS

Haproderm Gel is contraindicated in persons with a known hypersensitivity to any of the components of the formulation.

WARNINGS

Use only as directed. Keep out of the reach of children. Avoid contact with eyes. For topical use only. Not for ophthalmic use. Do not apply within four hours prior to a radiation session.

PRECAUTIONS AND OBSERVATIONS

- Haproderm Gel does not contain a sunscreen and should not be used prior to extended exposure to the sun.
- If clinical signs of infection are present, appropriate treatment should be initiated; use of Haproderm Gel may be continued during the anti-infective therapy.

INSTRUCTIONS FOR USE

Dispense Haproderm Gel into palm of hand and apply to affected area 3 times per day, or as directed by a physician. Massage gently into the skin until completely absorbed. If the skin is broken, cover with appropriate dressing Haproderm Gel is non-sterile.

INGREDIENTS

Allantoin
Aloe Barbadensis Leaf Extract
Caprylic/Capric Triglyceride
Carbomer
Ceteareth 20
Cetearyl Alcohol
Diazolidinyl Urea & Iodopropynyl Butylcarbamate
Dimethicone
Glycerin
Glycol Stearate
Hyaluronic Acid
Isopropyl Palmitate
Olea Europaea (Olive) Oil
Propylene Glycol
Tetrasodium EDTA
Triethanolamine
Water

HOW SUPPLIED

Haproderm Gel is available in 30g commercial pump dispenser.

CAUTION: Federal law restricts this device to sale by or on the order of a physician or other licensed health care practitioner.

Store between 59°F - 86°F (15°C - 30°C).

MANUFACTURED FOR:

NATIONAL BIO GREEN SCIENCES LIMITED LIABILITY COMPANY
Branchburg, NJ 08876

Label

HAPRODERM GEL

NET WEIGHT: 30G

NDC: 72678-020-07